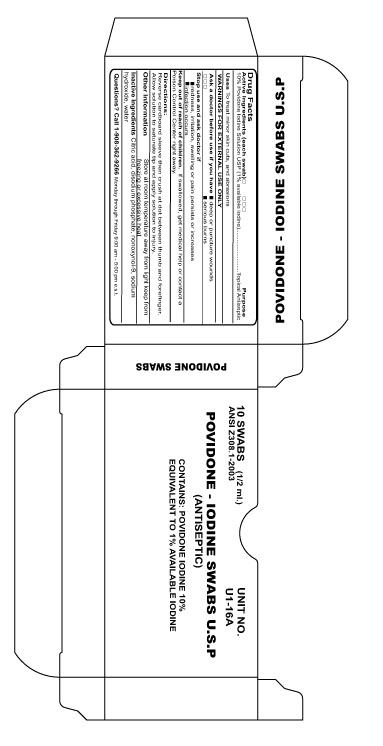 DRUG LABEL: Povidone Iodine
NDC: 68183-116 | Form: SWAB
Manufacturer: Custom Kits Company Inc
Category: otc | Type: HUMAN OTC DRUG LABEL
Date: 20200117

ACTIVE INGREDIENTS: POVIDONE-IODINE 10 mg/1 mL
INACTIVE INGREDIENTS: WATER

Povidone Iodine Swabs

Active Ingredient

10% Povidone Iodine Solution USP (1% available iodine)

Purpose

Topical Antiseptic

Directions

Reverse cardboard sleeve then crush at dot between thumb and forefinger. Allow solution to saturate tip and apply soltion to injury.

Warnings

- For External Use Only

Ask a Doctor before use if you have

Deep or puncture wounds

Serious Burns

Stop Use

redness, irritation, swelling or pain persists or increases

infection occurs

Keep Out Of Reach Of Children

If swallowed, get medical help or contact a Poison Control Center right away

Directions

Reverse cardboard sleeve then crush at dot between thumb and forefinger. Allow solution to saturate tip and apply solution to injury.

Other Information

Store at room temperature away from light keep from freezing or excessive heat

Inactive Ingredient

Citric acid, disodium phosphate, nonoxynol-9, sodium hydroxide, water